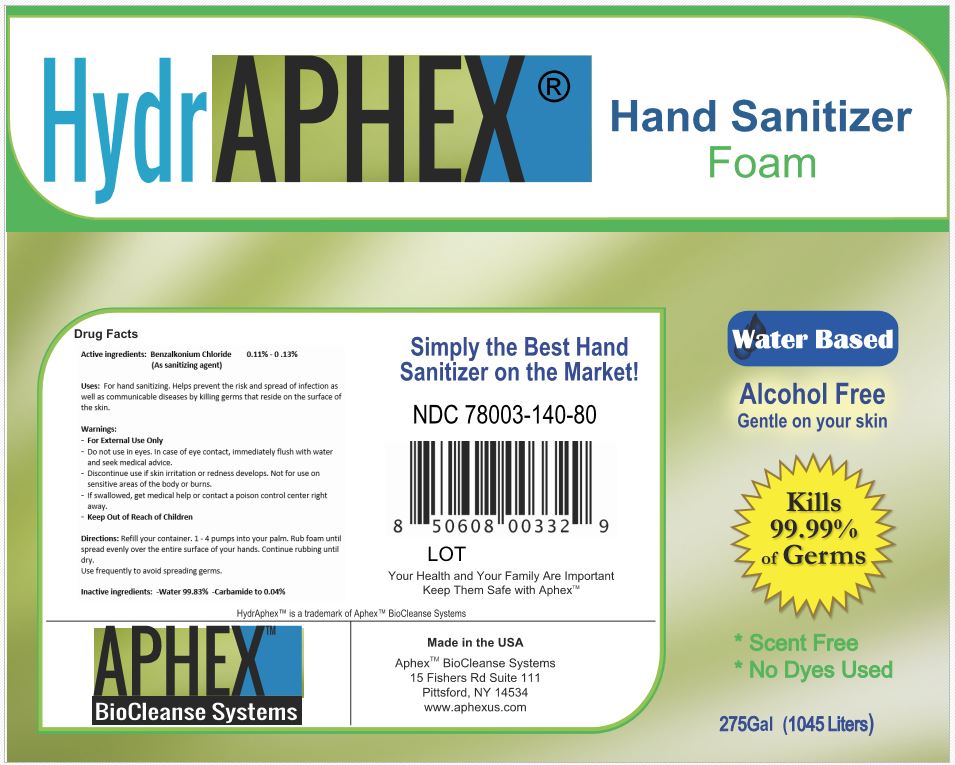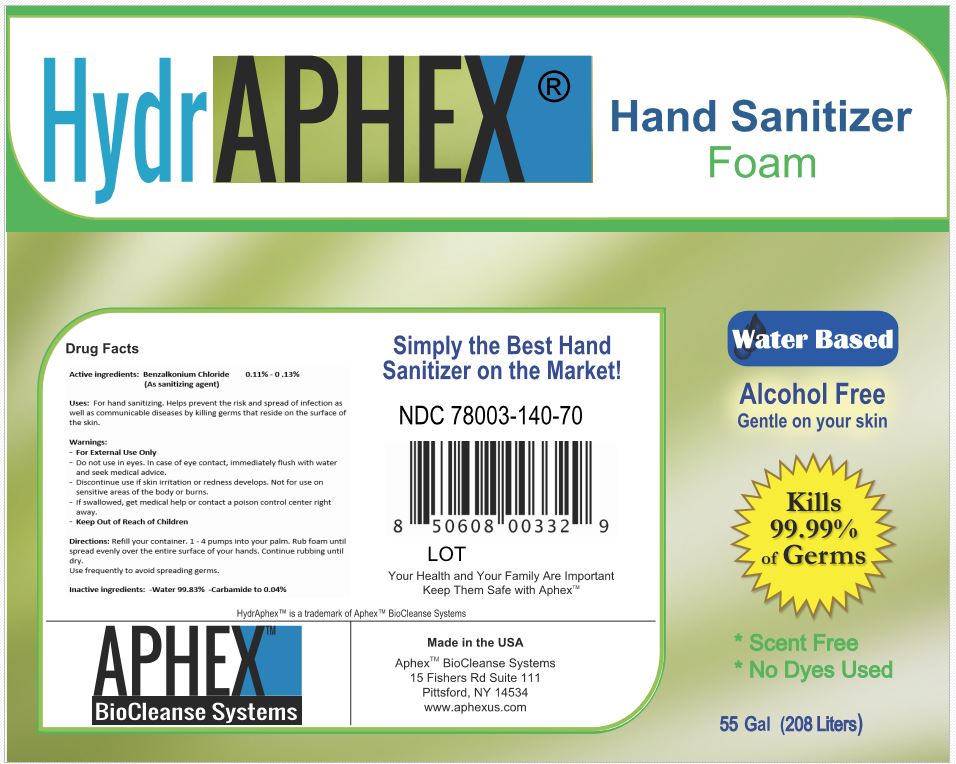 DRUG LABEL: HydrAphex
NDC: 78003-140 | Form: SOLUTION
Manufacturer: Aphex Biocleanse Systems, Inc
Category: otc | Type: HUMAN OTC DRUG LABEL
Date: 20220117

ACTIVE INGREDIENTS: BENZALKONIUM CHLORIDE 0.0013 g/1 mL
INACTIVE INGREDIENTS: WATER 1 mL/1 mL; UREA 0.0006 g/1 mL

HydrAphex Hand Sanitizer

Dosage and Admnstration

Directions: Refill your container. 1 - 4 pumps into your palm. Rub foam until spread evenly over the entire surface of your hands. Continue rubbing until dry.

Use frequently to avoid spreading germs.

Warnings

For External Use Only
Do not use in eyes. In case of eye contact, immediately flush with water and seek medical advice.
Discontinue use if skin irritation or redness develops. Not for use on sensitive areas of the body or burns.
If swallowed, get medical help or contact a poison control center right away.
Keep Out of Reach of Children

Inactive Ingredient

Inactive ingredients: -Water 99.83% -Carbamide to 0.04%

Usage Section

Uses: For hand sanitizing. Helps prevent the risk and spread of infection as well as communicable diseases by killing germs that reside on the surface of the skin.

Keep out of reach of Children

Active ingredient

Active ingredients: Benzalkonium Chloride 0.11% - 0 .13%

(As sanitizing agent)

Purpose Section

Active ingredients: Benzalkonium Chloride 0.11% - 0 .13%

(As sanitizing agent)